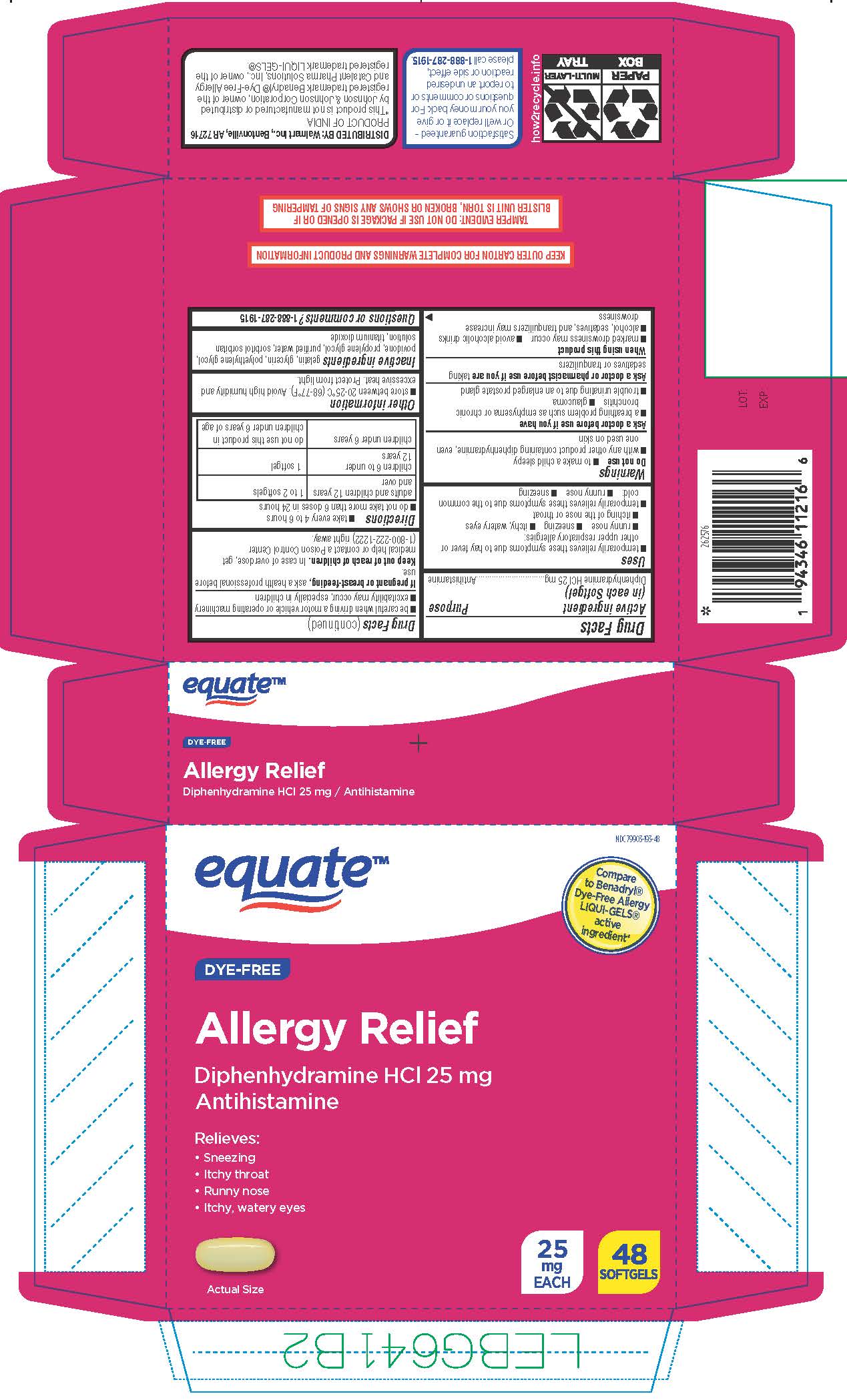 DRUG LABEL: Allergy Relief
NDC: 79903-193 | Form: CAPSULE, LIQUID FILLED
Manufacturer: Wal-Mart Stores Inc
Category: otc | Type: HUMAN OTC DRUG LABEL
Date: 20260126

ACTIVE INGREDIENTS: DIPHENHYDRAMINE HYDROCHLORIDE 25 mg/1 1
INACTIVE INGREDIENTS: GELATIN; GLYCERIN; POLYETHYLENE GLYCOL 400; POVIDONE; PROPYLENE GLYCOL; WATER; SORBITOL; TITANIUM DIOXIDE

Dye-Free Allergy Relief

Active ingredient (in each capsule)

Diphenhydramine HCl 25 mg

Purpose

Antihistamine

Uses

- temporarily relieves these symptoms due to hay fever or other upper respiratory allergies: sneezing, runny nose, itchy, watery eyes, itching of the nose or throat
- temporarily relieves these symptoms due to hay fever or other upper respiratory allergies: sneezing, runny nose

Warnings

Do not use

- with any other product containing diphenhydramine, even one used on skin
- to make a child sleepy

Ask a doctor before use if you have

- glaucoma
- trouble urinating due to an enlarged prostate gland
- a breathing problem such as emphysema or chronic bronchitis

Ask a doctor or pharmacist before use if you are

taking sedatives or tranquilizers.

When using this product

- marked drowsiness may occur
- avoid alcoholic drinks
- alcohol, sedatives, and tranquilizers may increase drowsiness
- be careful when driving a motor vehicle or operating machinery
- excitability may occur, especially in children

If pregnant or breast-feeding,

ask a health professional before use.

Keep out of reach of children.

In case of overdose, get medical help or contact a Poison Control Center right away. (1-800-222-1222)

Directions

- take every 4 to 6 hours
- do not take more than 6 doses in 24 hours
- swallow whole; do not crush, chew or dissolve
- adults and children 12 years of age and over - take 1 to 2 softgels
- children 6 to under 12 years of age - take 1 softgel
- children under 6 years of age - do not use

Other information

- store between 20-25ºC (68 to 77°F). Avoid high humidityandexcessive heat.
- Protect from light, heat, humidity

Inactive ingredients

gelatin, glycerin, polyethylene glycol, povidone, propylene glycol, purified water, sorbitol-sorbitan solution, titanium dioxide

Questions or comments?

Call 1-888-287-1915